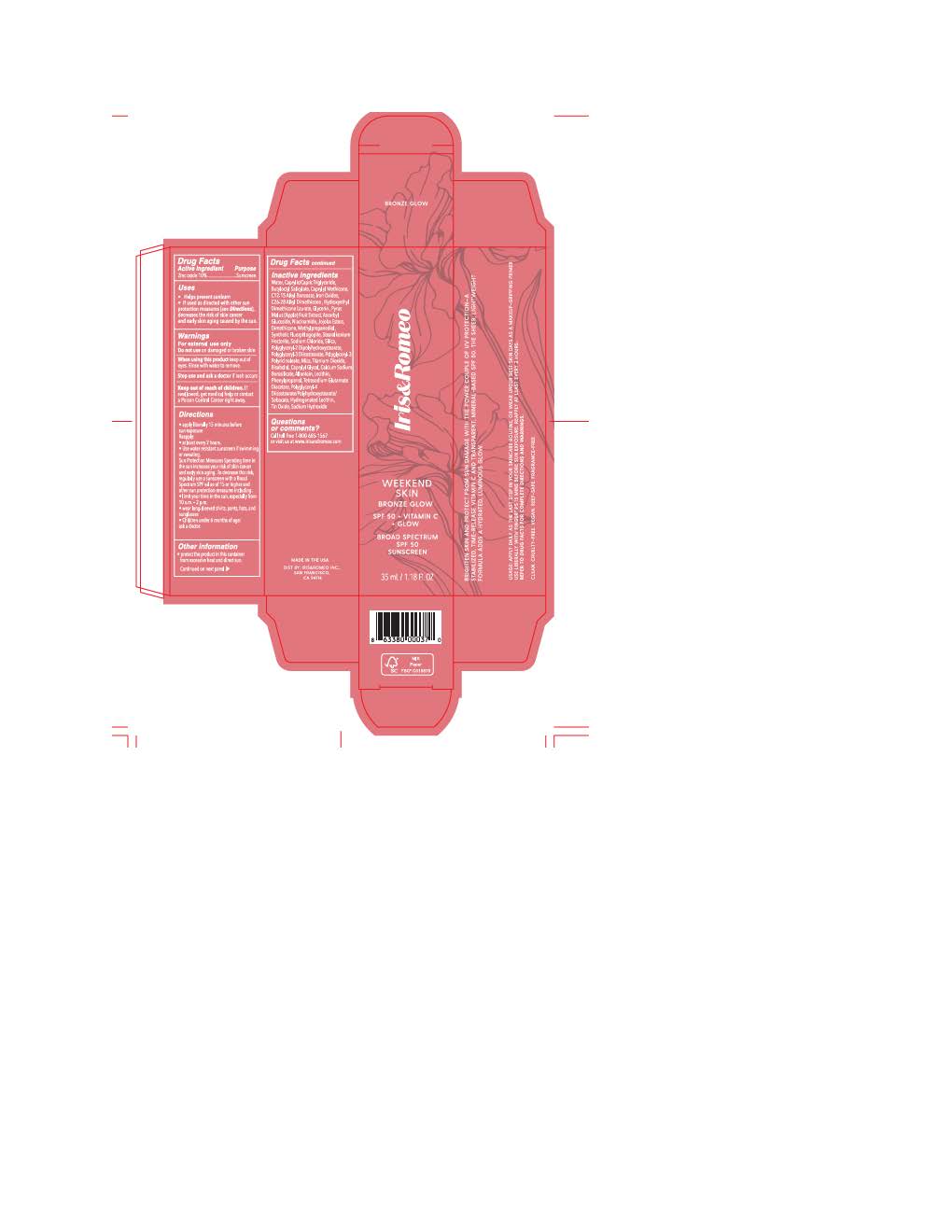 DRUG LABEL: Iris and Romeo Weekend Skin Bronze Glow
NDC: 83247-2195 | Form: LOTION
Manufacturer: Iris and Romeo
Category: otc | Type: HUMAN OTC DRUG LABEL
Date: 20251031

ACTIVE INGREDIENTS: ZINC OXIDE 110 mg/1 mL
INACTIVE INGREDIENTS: PHENYLPROPANOL; STEARALKONIUM HECTORITE; .ALPHA.-BISABOLOL, (+)-; ALLANTOIN; CAPRYLYL GLYCOL; POLYGLYCERYL-4 DIISOSTEARATE/POLYHYDROXYSTEARATE/SEBACATE; WATER; TETRASODIUM GLUTAMATE DIACETATE; SODIUM CHLORIDE; FERRIC OXIDE RED; ALKYL (C12-15) BENZOATE; DIMETHICONE; FERROSOFERRIC OXIDE; FERRIC OXIDE YELLOW; TITANIUM DIOXIDE; HYDROGENATED SOYBEAN LECITHIN; SODIUM HYDROXIDE; BUTYLOCTYL SALICYLATE; NIACINAMIDE; CAPRYLIC/CAPRIC TRIGLYCERIDE; GLYCERIN; PYRUS MALUS (APPLE) FRUIT; CALCIUM SODIUM BOROSILICATE; TIN OXIDE; POLYGLYCERYL-3 DIISOSTEARATE; ASCORBYL GLUCOSIDE; SILICON DIOXIDE; POLYGLYCERYL-2 DIPOLYHYDROXYSTEARATE; HYDROLYZED JOJOBA ESTERS (ACID FORM); METHYLPROPANEDIOL; MICA

Iris and Romeo Weekend Skin Bronze Glow